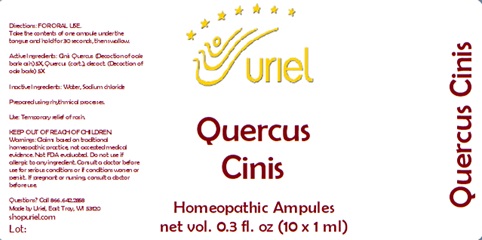 DRUG LABEL: Quercus Cinis
NDC: 48951-8117 | Form: LIQUID
Manufacturer: Uriel Pharmacy Inc.
Category: homeopathic | Type: HUMAN OTC DRUG LABEL
Date: 20241203

ACTIVE INGREDIENTS: QUERCUS ROBUR WHOLE 5 [hp_X]/1 mL
INACTIVE INGREDIENTS: SODIUM CHLORIDE; WATER

Quercus Cinis

INDICATIONS AND USAGE

Directions: FOR ORAL USE.

DOSAGE AND ADMINISTRATION

Take the contents of one ampule under the tongue and hold for 30 seconds, then swallow.

ACTIVE INGREDIENT

Active Ingredients: Cinis Quercus (Decoction of oak bark ash) 5X, Quercus (cort.), decoct. (Decoction of oak bark) 5X

Inactive Ingredients: Water, Sodium chloride

Prepared using rhythmical processes.

PURPOSE

Use: Temporary relief of rash.

KEEP OUT OF REACH OF CHILDREN.

WARNINGS

Warnings: Claims based on traditional homeopathic practice, not accepted medical evidence. Not FDA evaluated. Do not use if allergic to any ingredient. Consult a doctor before use for serious conditions or if conditions worsen or persist. If pregnant or nursing, consult a doctor before use.

QUESTIONS

Questions? Call 866.642.2858 Made by Uriel, East Troy, WI 53120 shopuriel.com Lot: